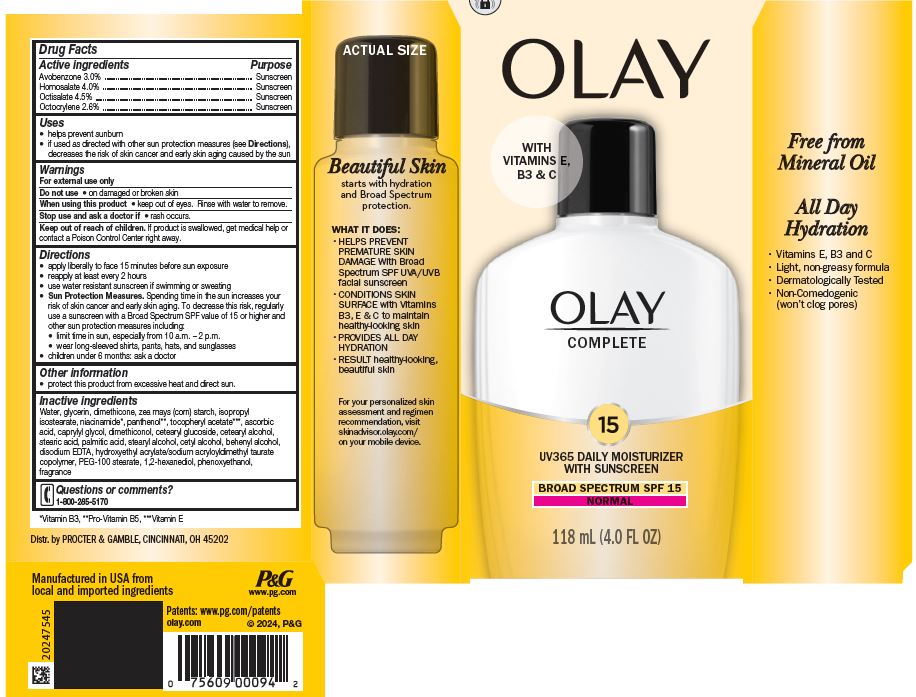 DRUG LABEL: Olay Complete UV 365 Daily Moisturizer Normal
NDC: 69423-195 | Form: LOTION
Manufacturer: The Procter & Gamble Manufacturing Company
Category: otc | Type: HUMAN OTC DRUG LABEL
Date: 20251218

ACTIVE INGREDIENTS: AVOBENZONE 3 g/100 mL; HOMOSALATE 4 g/100 mL; OCTISALATE 4.5 g/100 mL; OCTOCRYLENE 2.6 g/100 mL
INACTIVE INGREDIENTS: HYDROXYETHYL ACRYLATE/SODIUM ACRYLOYLDIMETHYL TAURATE COPOLYMER (45000 MPA.S AT 1%); PEG-100 STEARATE; 1,2-HEXANEDIOL; CAPRYLYL GLYCOL; STARCH, CORN; WATER; GLYCERIN; DIMETHICONOL (50000 CST); DIMETHICONE; NIACINAMIDE; PANTHENOL; .ALPHA.-TOCOPHEROL ACETATE; STEARIC ACID; CETEARYL GLUCOSIDE; CETOSTEARYL ALCOHOL; ASCORBIC ACID; CETYL ALCOHOL; STEARYL ALCOHOL; DOCOSANOL; PHENOXYETHANOL; PALMITIC ACID; EDETATE DISODIUM; ISOPROPYL ISOSTEARATE

Olay® Complete UV365 - Normal
Moisturizer Broad Spectrum SPF 15 Normal

Drug Facts

ACTIVE INGREDIENT

Avobenzone 3.0%
Homosalate 4.0%
Octisalate 4.5%
Octocrylene 2.6%

PURPOSE

Sunscreen

Uses

- helps prevent sunburn
- if used as directed with other sun protection measures (see Directions), decreases the risk of skin cancer and early skin aging caused by the sun

Warnings

For external use only

Do not use on damaged or broken skin

When using this product keep out of eyes. Rinse with water to remove.

Stop use and ask a doctor if rash occurs

Keep out of reach of children. If product is swallowed, get medical help or contact a Poison Control Center right away.

Directions

- apply liberally 15 minutes before sun exposure
- reapply at least every 2 hours
- use water resistant sunscreen if swimming or sweating
- Sun Protection Measures. Spending time in the sun increases your risk of skin cancer and early skin aging. To decrease this risk, regularly use a sunscreen with a Broad Spectrum SPF value of 15 or higher and other sun protection measures including:
  - limit time in sun, especially from 10 a.m. – 2 p.m.
  - wear long-sleeved shirts, pants, hats, and sunglasses
- children under 6 months: ask a doctor

Other information

- protect this product from excessive heat and direct sun

Inactive ingredients

Water, glycerin, dimethicone, zea mays (corn) starch, isopropyl isostearate, niacinamide, panthenol, tocopheryl acetate, ascorbic acid, caprylyl glycol, dimethiconol, cetearyl glucoside, cetearyl alcohol, stearic acid, palmitic acid, stearyl alcohol, cetyl alcohol, behenyl alcohol, disodium EDTA, hydroxyethyl acrylate/sodium acryloyldimethyl taurate copolymer, PEG-100 stearate, 1,2-hexanediol, phenoxyethanol, fragrance

Questions or comments?

Call 1-800-285-5170

www.olay.com

Dist. by
PROCTER & GAMBLE,
CINCINNATI, OH 45202

PRINCIPAL DISPLAY PANEL - 118 mL Bottle Carton

OLAY®

complete

15

UV 365 Daily Moisturizer
with sunscreen

BROAD SPECTRUM SPF 15
NORMAL

118 mL (4.0 FL OZ)